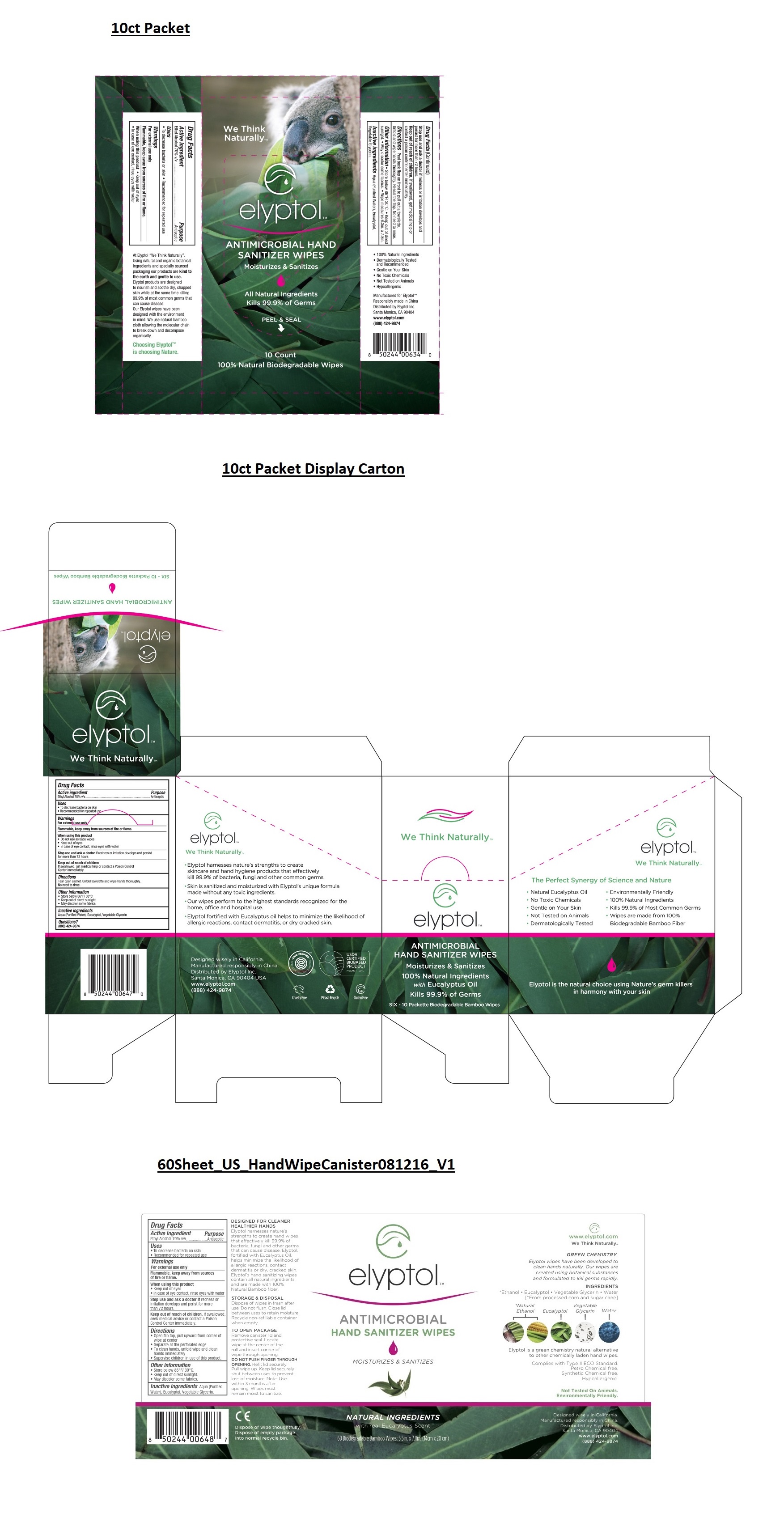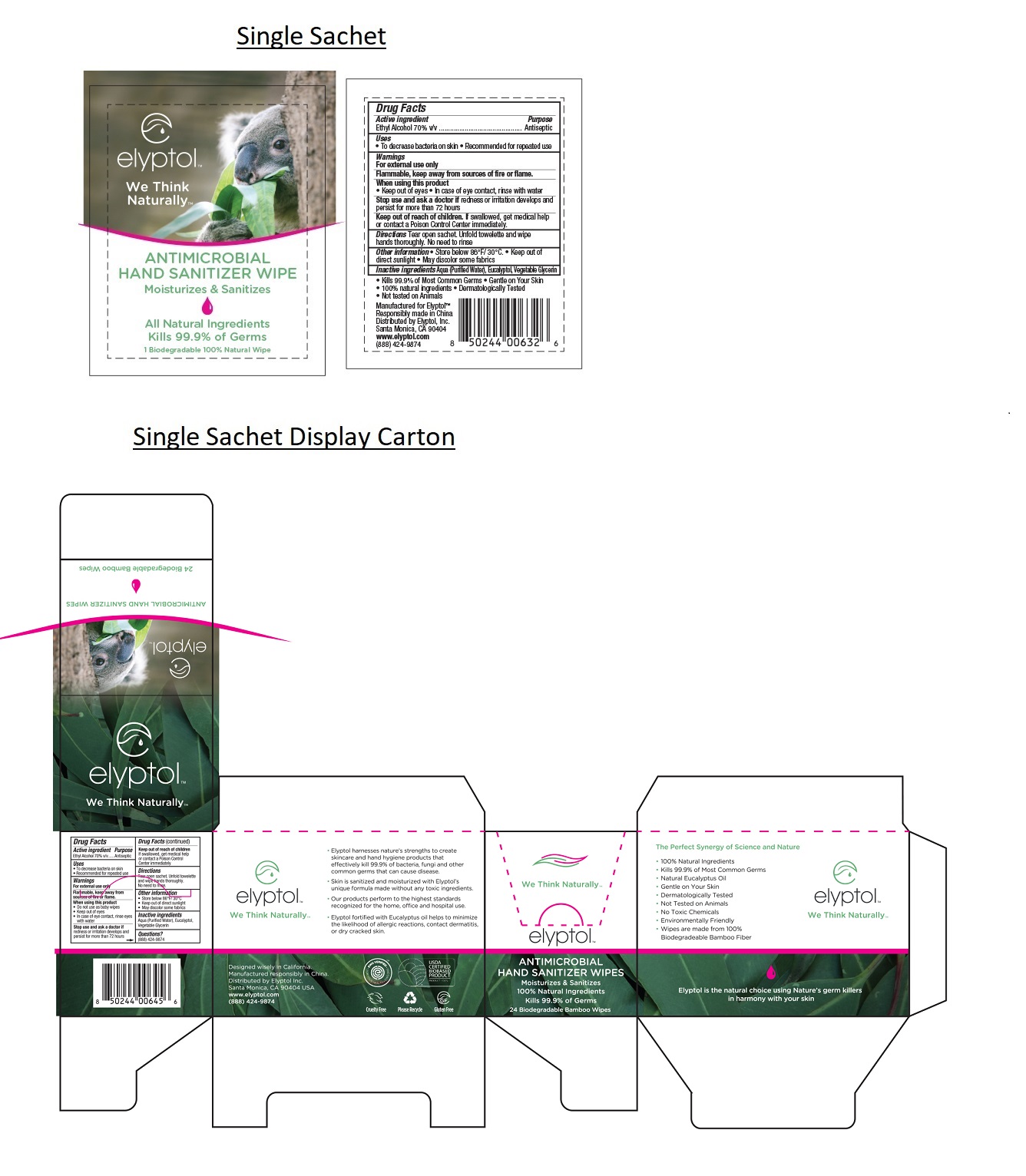 DRUG LABEL: Elyptol Hand Sanitizer Wipe
NDC: 69343-322 | Form: CLOTH
Manufacturer: Elyptol Inc.
Category: otc | Type: HUMAN OTC DRUG LABEL
Date: 20211222

ACTIVE INGREDIENTS: ALCOHOL 0.7 1/1 1
INACTIVE INGREDIENTS: WATER; GLYCERIN

Elyptol Hand Sanitizer Wipes - Sachet Wipes

Drug Facts

Active Ingredients

Ethyl Alcohol 70% v/v

Inactive Ingredients

Aqua (Purified Water), Eucalyptol, Glyercin

Purpose

Skin antiseptic

Warnings

For external use only.

Flammable.. Keep away from sources of fire or flame.

When using this product

Keep away from eyes. In case of eye contact, rinse eyes with water.

Stop use and ask a doctor if

redness or irritation develops and issues persist, seek medical attention.

Directions

- Tear open sachet.
- Unfold towelette and wipe hands thoroughly.
- No need to rinse.

Keep out of reach of children.

Other Information

- Store below 86F / 30C
- Keep out of direct sunlight
- May discolor some fabrics
- Lot No. and Expiration Date can be found on packet

Uses

- To decrease bacteria on skin.
- Recommended for repeated use.

Questions? (888) 424-9874

- 100% biobased ingredients
- Kills 99.9% of Most Common Germs
- Pure Eucalyptus Oil • Gentle on Your Skin
- Dermatologically Tested • Not tested on Animals